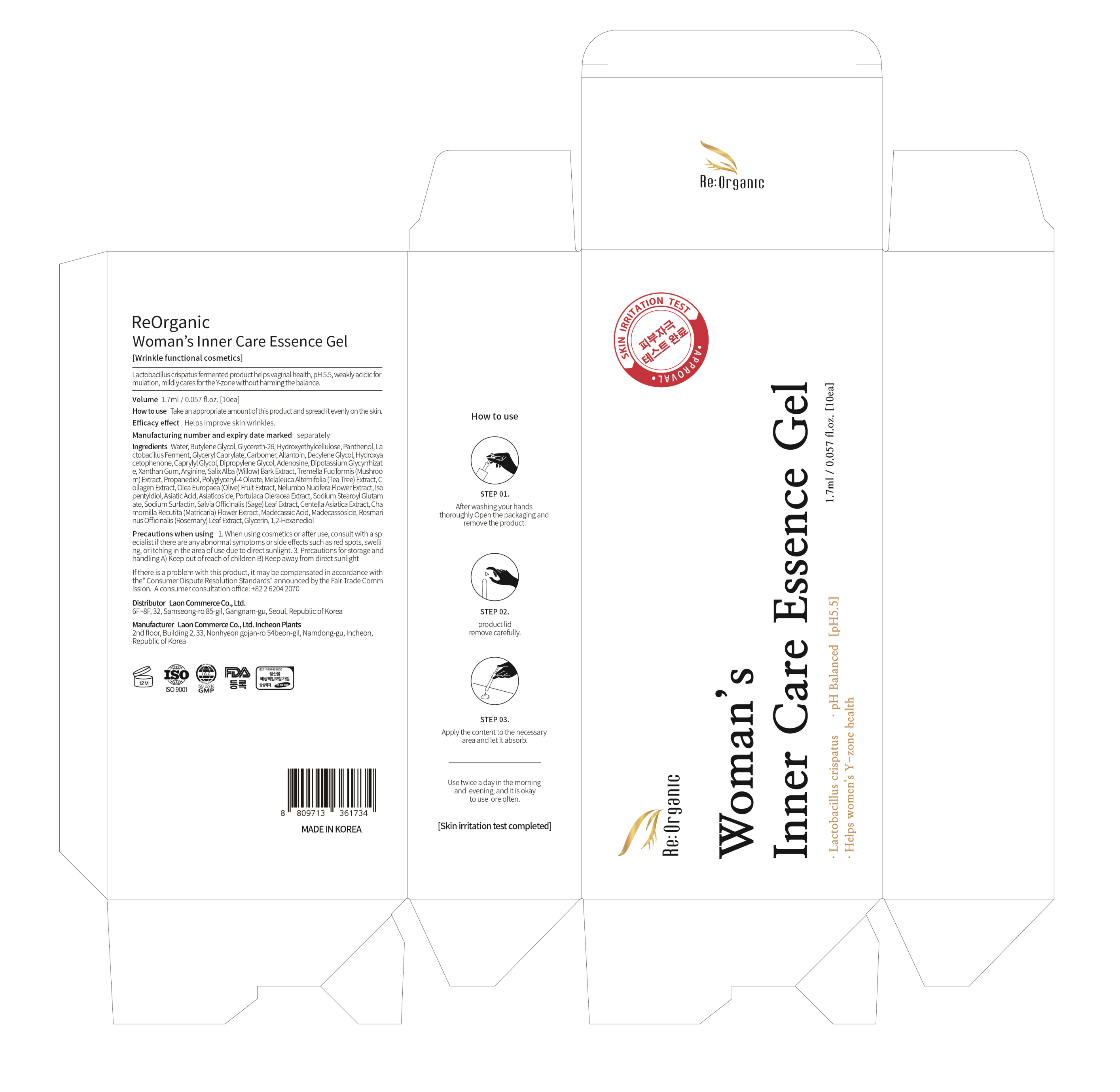 DRUG LABEL: ReOrganic Womans Inner Care Essence Gel
NDC: 82083-0018 | Form: GEL
Manufacturer: LAON COMMERCE co ltd
Category: otc | Type: HUMAN OTC DRUG LABEL
Date: 20230525

ACTIVE INGREDIENTS: ADENOSINE 0.04 g/100 mL
INACTIVE INGREDIENTS: PANTHENOL; ALLANTOIN

ACTIVE INGREDIENT

Adenosine

INACTIVE INGREDIENT

Water
Butylene Glycol
Glycereth-26
Hydroxyethylcellulose
Panthenol
Lactobacillus Ferment
Glyceryl Caprylate
Carbomer
Allantoin
Decylene Glycol
Hydroxyacetophenone
Caprylyl Glycol
Dipropylene Glycol
Dipotassium Glycyrrhizate
Xanthan Gum
Arginine
Salix Alba (Willow) Bark Extract
Tremella Fuciformis (Mushroom) Extract
Propanediol
Polyglyceryl-4 Oleate
Melaleuca Alternifolia (Tea Tree) Extract
Collagen Extract
Olea Europaea (Olive) Fruit Extract
Nelumbo Nucifera Flower Extract
Isopentyldiol
Asiatic Acid
Asiaticoside
Portulaca Oleracea Extract
Sodium Stearoyl Glutamate
Sodium Surfactin
Salvia Officinalis (Sage) Leaf Extract
Centella Asiatica Extract
Chamomilla Recutita (Matricaria) Flower Extract
Madecassic Acid
Madecassoside
Rosmarinus Officinalis (Rosemary) Leaf Extract
Glycerin
1,2-Hexanediol

PURPOSE

skin protect

KEEP OUT OF REACH OF THE CHILDREN

INDICATIONS AND USAGE

Take an appropriate amount of this product and spread it evenly on the skin

WARNINGS

1. When using cosmetics or after use, consult with a sp ecialist if there are any abnormal symptoms or side effects such as red spots, swelli ng, or itching in the area of use due to direct sunlight. 3. Precautions for storage and handling A) Keep out of reach of children B) Keep away from direct sunlight

DOSAGE AND ADMINISTRATION

topical use only